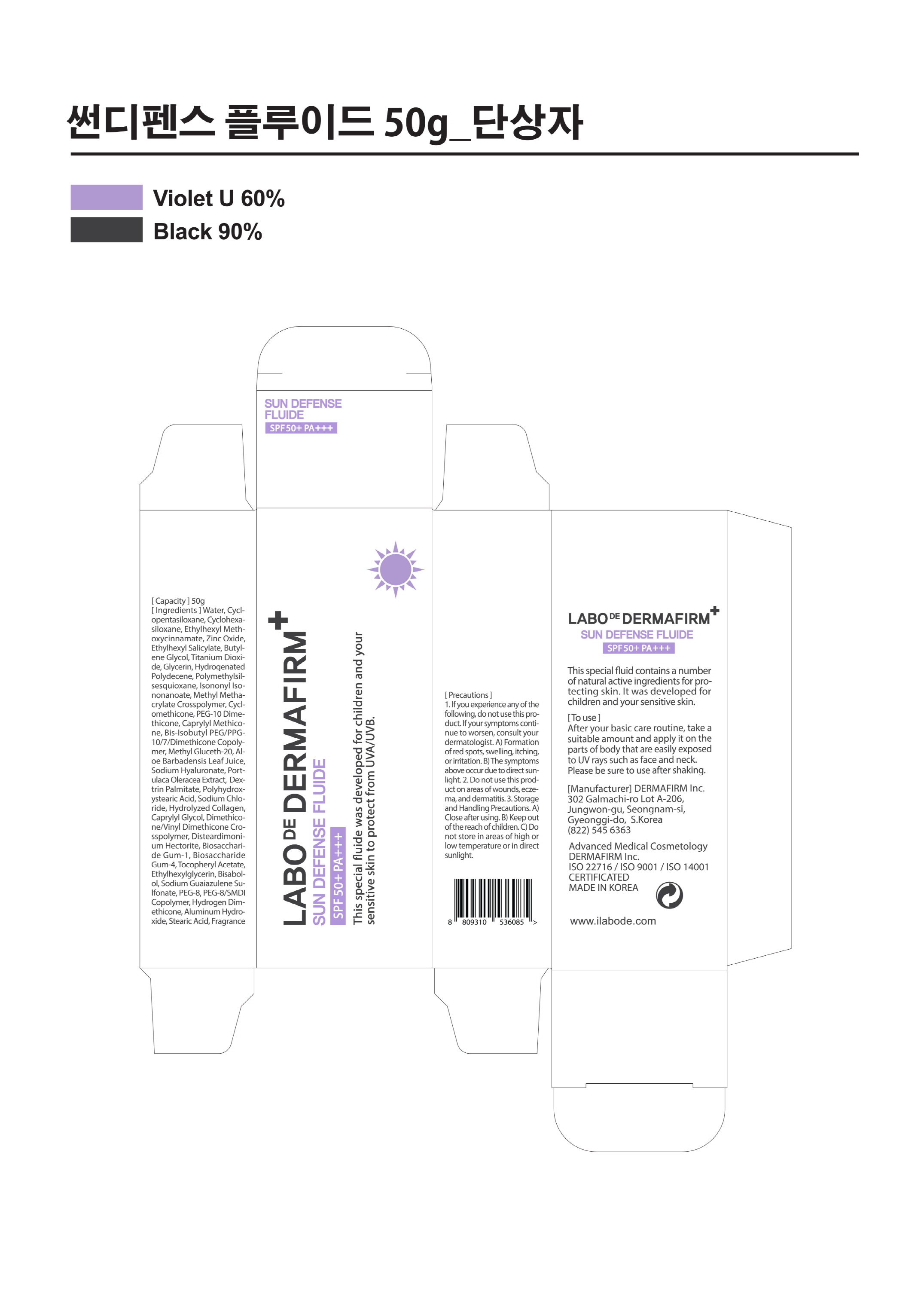 DRUG LABEL: Labo De Dermafirm Sun Defense Fluid
NDC: 71638-0012 | Form: LIQUID
Manufacturer: Dermafirm INC.
Category: otc | Type: HUMAN OTC DRUG LABEL
Date: 20180525

ACTIVE INGREDIENTS: ZINC OXIDE 5.52 g/100 g; OCTISALATE 5 g/100 g; TITANIUM DIOXIDE 4.15 g/100 g; OCTINOXATE 7.5 g/100 g
INACTIVE INGREDIENTS: WATER; GLYCERIN

Drug Facts

ACTIVE INGREDIENT

ETHYLHEXYL METHOXYCINNAMATE, ZINC OXIDE, ETHYLHEXYL SALICYLATE, TITANIUM DIOXIDE

INACTIVE INGREDIENT

Water, Glycerin, ETC

PURPOSE

Sunscreen

keep out of reach of the children

INDICATIONS AND USAGE

▶ After basic skin care, apply on entire face and neck.
▶ Apply before sun exposure.
▶ Apply often to sun-sensitive areas

WARNINGS

1. Do not use in the following cases(Eczema and scalp wounds)
2.Side Effects
1)Due to the use of this druf if rash, irritation, itching and symptopms of hypersnesitivity occur dicontinue use and consult your phamacisr or doctor
3.General Precautions
1)If in contact with the eyes, wash out thoroughty with water If the symptoms are servere, seek medical advice immediately
2)This product is for exeternal use only. Do not use for internal use
4.Storage and handling precautions
1)If possible, avoid direct sunlight and store in cool and area of low humidity
2)In order to maintain the quality of the product and avoid misuse
3)Avoid placing the product near fire and store out in reach of children

DOSAGE AND ADMINISTRATION

for external use only